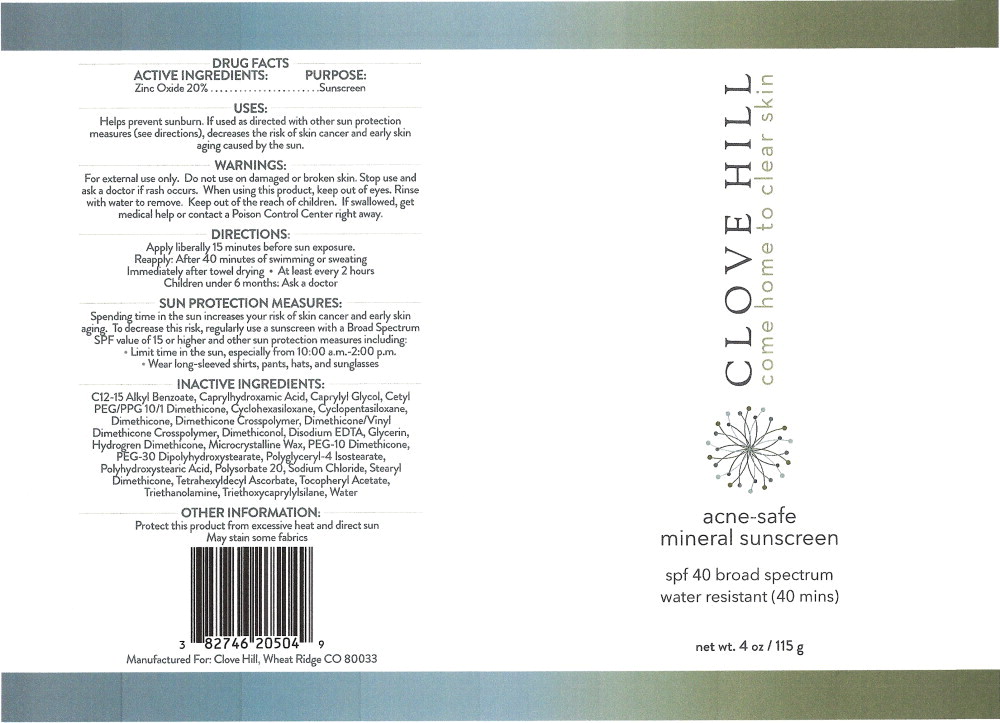 DRUG LABEL: Clove Hill acne safe mineral sunscreen SPF 40
NDC: 82746-205 | Form: CREAM
Manufacturer: Clove Hill LLC
Category: otc | Type: HUMAN OTC DRUG LABEL
Date: 20240122

ACTIVE INGREDIENTS: Zinc Oxide 200 mg/1 g
INACTIVE INGREDIENTS: ALKYL (C12-15) BENZOATE; CAPRYLHYDROXAMIC ACID; CAPRYLYL GLYCOL; CETYL PEG/PPG-10/1 DIMETHICONE (HLB 5); CYCLOMETHICONE 6; CYCLOMETHICONE 5; DIMETHICONE 100; DIMETHICONE CROSSPOLYMER (450000 MPA.S AT 12% IN CYCLOPENTASILOXANE); DIMETHICONE/VINYL DIMETHICONE CROSSPOLYMER (SOFT PARTICLE); DIMETHICONOL (2000 CST); EDETATE DISODIUM; GLYCERIN; HYDROGEN DIMETHICONE (20 CST); MICROCRYSTALLINE WAX; PEG-10 DIMETHICONE (600 CST); PEG-30 DIPOLYHYDROXYSTEARATE (4000 MW); POLYGLYCERYL-4 ISOSTEARATE; POLYHYDROXYSTEARIC ACID (2300 MW); POLYSORBATE 20; SODIUM CHLORIDE; STEARYL DIMETHICONE (400 MPA.S AT 50C); TETRAHEXYLDECYL ASCORBATE; .ALPHA.-TOCOPHEROL ACETATE; TROLAMINE; TRIETHOXYCAPRYLYLSILANE; WATER

DRUG FACTS

ACTIVE INGREDIENTS:

Zinc Oxide 20%

PURPOSE:

Sunscreen

USES:

Helps prevent sunburn. If used as directed with other sun protection measures (see directions), decreases the risk of skin cancer and early skin aging caused by the sun.

WARNINGS:

For external use only. Do not use on damaged or broken skin. Stop use and ask a doctor if rash occurs. When using this product, keep out of eyes. Rinse with water to remove.

KEEP OUT OF REACH OF CHILDREN

Keep out of the reach of children. If swallowed, get medical help or contact a Poison Control Center right away.

DIRECTIONS:

Apply liberally 15 minutes before sun exposure.

Reapply: After 40 minutes of swimming or sweating

Immediately after towel drying • At least every 2 hours

Children under 6 months: Ask a doctor

SUN PROTECTION MEASURES:

Spending time in the sun increases your risk of skin cancer and early skin aging. To decrease this risk, regularly use a sunscreen with a Broad Spectrum SPF value of 15 or higher and other sun protection measures including:

- Limit time in the sun, especially from 10:00 a.m.-2:00 p.m.
- Wear long-sleeved snirts, pants, hats, and sunglasses

INACTIVE INGREDIENTS:

C12-15 Alkyl Benzoate, Caprylhydroxamic Acid, Caprylyl Glycol, Cetyl PEG/PPG10/1 Dimethicone, Cyclohexasiloxane, Cyclopentasiloxane, Dimethicone, Dimethicone Crosspolymer, Dimethicone/Vinyl Dimethicone Crosspolymer, Dimethiconol, Disodium EDTA, Glycerin, Hydrogren Dimethicone, Microcrystalline Wax, PEG-10 Dimethicone, PEG-30 Dipolyhydroxystearate, Polyglyceryl-4 Isostearate, Polyhydroxystearic Acid, Polysorbate 20, Sodium Chloride, Stearyl Dimethicone, Tetrahexyldecyl Ascorbate, Tocopheryl Acetate, Triethanolamine, Triethoxycaprylylsilane, Water

OTHER INFORMATION:

Protect this product from excessive heat and direct sun

May stain some fabrics

Principal Display Panel – 115 g Bottle Label

CLOVE HILL

come home to clear skin

acne-safe
mineral sunscreen

spf 40 broad spectrum

water resistant (40 mins)

net wt. 4 oz /115 g